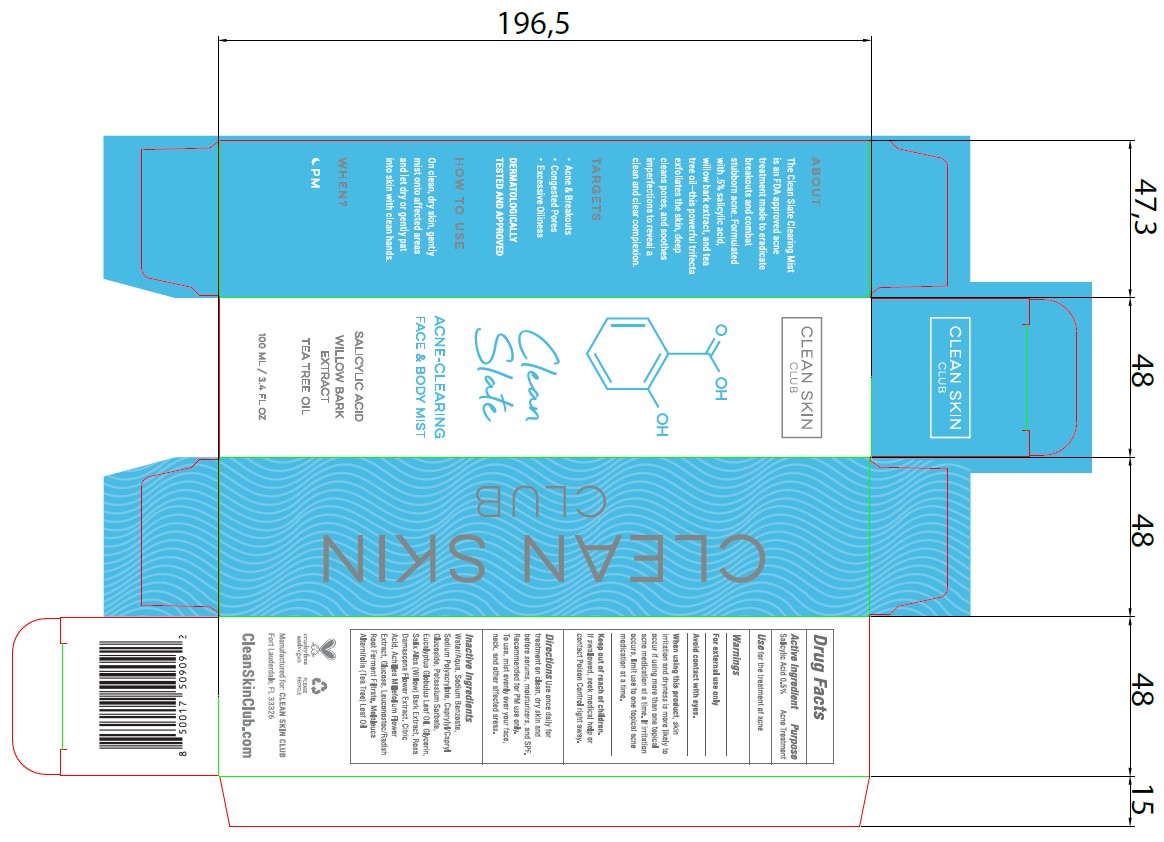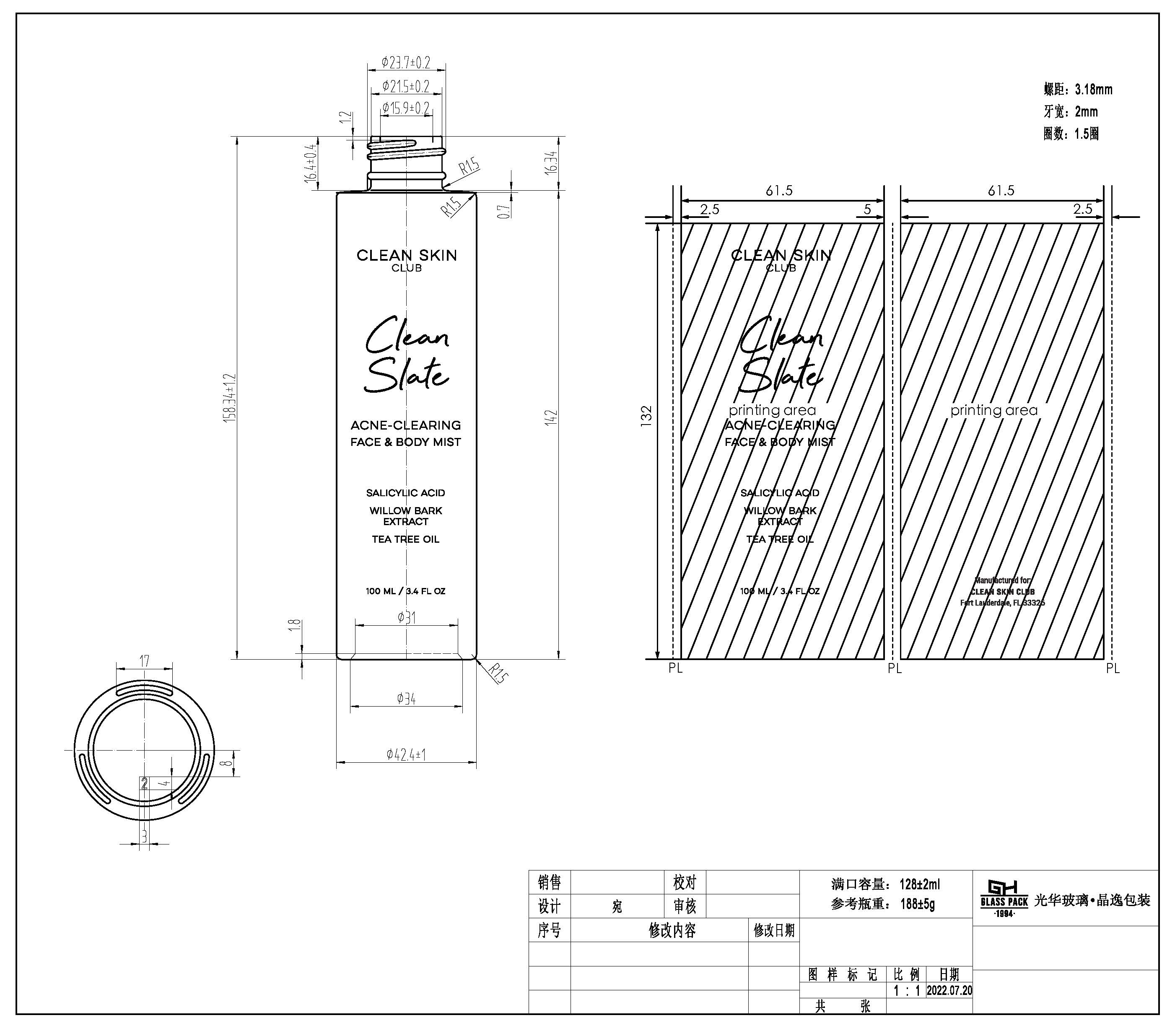 DRUG LABEL: MIST
NDC: 61354-092 | Form: LIQUID
Manufacturer: OXYGEN DEVELOPMENT, LLC
Category: otc | Type: HUMAN OTC DRUG LABEL
Date: 20230614

ACTIVE INGREDIENTS: SALICYLIC ACID 0.5 mg/100 mg
INACTIVE INGREDIENTS: LEUCONOSTOC/RADISH ROOT FERMENT FILTRATE; MELALEUCA ALTERNIFOLIA LEAF; WATER; SALIX ALBA BARK; POTASSIUM SORBATE; EUCALYPTUS GLOBULUS LEAF; GLYCERIN; CAPRYLYL/CAPRYL OLIGOGLUCOSIDE; ROSA DAMASCENA FLOWER; ACHILLEA MILLEFOLIUM FLOWER; SODIUM BENZOATE; SODIUM POLYACRYLATE (8000 MW)

CLEAN SKIN CLUB CLEAN SLATE CLEARING MIST

Active Ingredient

Salicylic Acid.... 0.5%

Purpose

Acne Treatment

Use

Use for treatment of acne

Warnings

For external use only

Avoid contact with eyes

Contact with eyes

Avoid contact with eyes

When using this product, skin irritation and dryness is more likely to occur if using more than one topical acne medication at a time. If irritation occurs, limit use to one topical acne medication at a time.

Keep out of reach of children. If swallowed, seek medical help or contact Poison Control right away.

Directions

Use once daily for treatment on clean, dry skin and before serums, moisturizers, and SPF. Recommended for PM use only. To use, mist evenly over your face, neck, and other affected areas.

Inactive Ingredients

Water/Aqua, Sodium Benzoate, Sodium Polyacrylate, Caprylyl/Capryl Glucoside, Potassium Sorbate, Eucalyptus Globulus Leaf Oil, Glycerin, Salix Alba (Willow) Bark Extract, Rosa Damascena Flower Extract, Citric Acid, achillea Milefolium Flower Extract, Glucose, Leuconostoc/Radish Root Ferment Filtrate, Melaleuca Alternifolia (Tea Tree) Leaf Oil.

When using this product, skin irritation, and dryness is more likely to occur if using more than one topical acne medication at a time. If irritation occurs, limit use to one topical acne medication at a time.

Keep out of reach of children

If swallowed, seek medical help or contact Poison Control right away